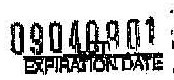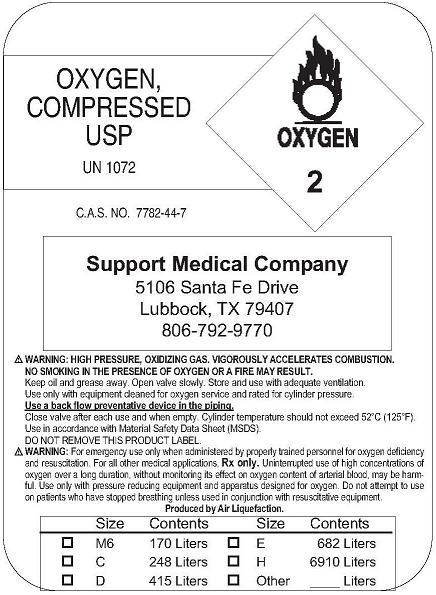 DRUG LABEL: Oxygen
NDC: 43276-0001 | Form: GAS
Manufacturer: Support Medical Company
Category: prescription | Type: HUMAN PRESCRIPTION DRUG LABEL
Date: 20091028

ACTIVE INGREDIENTS: Oxygen 99 L/100 L

Oxygen